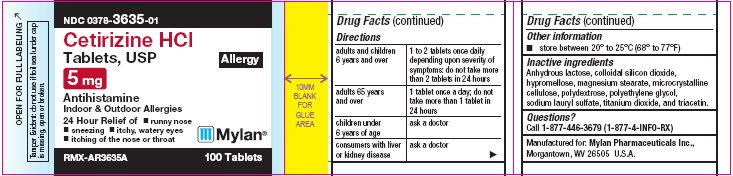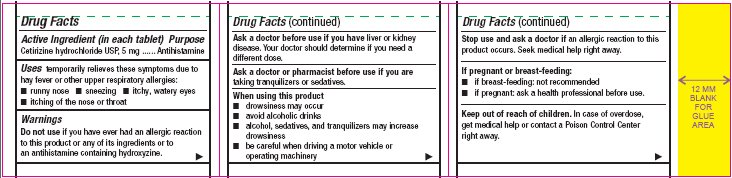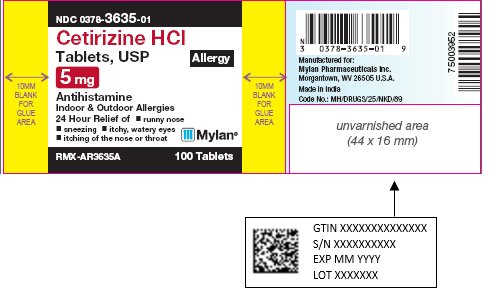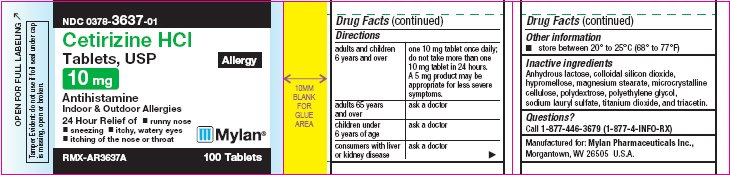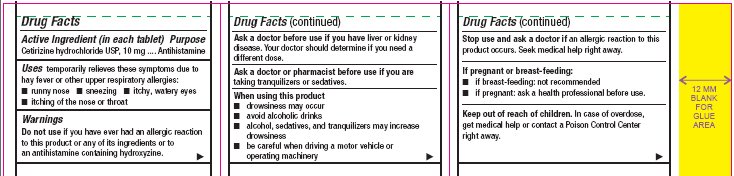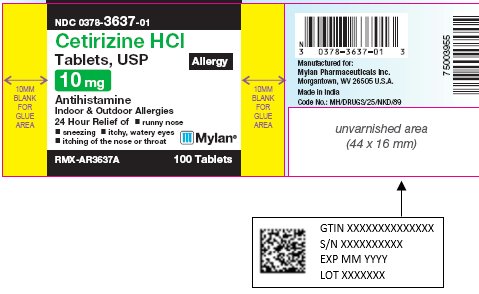 DRUG LABEL: Cetirizine Hydrochloride
NDC: 0378-3635 | Form: TABLET, FILM COATED
Manufacturer: Mylan Pharmaceuticals Inc.
Category: otc | Type: HUMAN OTC DRUG LABEL
Date: 20220112

ACTIVE INGREDIENTS: CETIRIZINE HYDROCHLORIDE 5 mg/1 1
INACTIVE INGREDIENTS: ANHYDROUS LACTOSE; SILICON DIOXIDE; HYPROMELLOSE, UNSPECIFIED; MAGNESIUM STEARATE; MICROCRYSTALLINE CELLULOSE; POLYDEXTROSE; POLYETHYLENE GLYCOL, UNSPECIFIED; SODIUM LAURYL SULFATE; TITANIUM DIOXIDE; TRIACETIN

Drug Facts

Active Ingredient (in each tablet)

Cetirizine hydrochloride USP, 5 mg

Purpose

Antihistamine

Uses

temporarily relieves these symptoms due to hay fever or other upper respiratory allergies:

- runny nose
- sneezing
- itchy, watery eyes
- itching of the nose or throat

Warnings

Do not use

if you have ever had an allergic reaction to this product or any of its ingredients or to an antihistamine containing hydroxyzine.

Ask a doctor before use if you have

liver or kidney disease. Your doctor should determine if you need a different dose.

Ask a doctor or pharmacist before use if you are

taking tranquilizers or sedatives.

When using this product

- drowsiness may occur
- avoid alcoholic drinks
- alcohol, sedatives, and tranquilizers may increase drowsiness
- be careful when driving a motor vehicle or operating machinery

Stop use and ask a doctor if

an allergic reaction to this product occurs. Seek medical help right away.

If pregnant or breast-feeding:

- if breast-feeding: not recommended
- if pregnant: ask a health professional before use.

Keep out of reach of children.

In case of overdose, get medical help or contact a Poison Control Center right away.

Directions

adults and children 6 years and over | 1 to 2 tablets once daily depending upon severity of symptoms; do not take more than 2 tablets in 24 hours.
adults 65 years and over | 1 tablet once a day; do not take more than 1 tablet in 24 hours
children under 6 years of age | ask a doctor
consumers with liver or kidney disease | ask a doctor

Other information

- store between 20° to 25°C (68° to 77°F)

Inactive ingredients

Anhydrous lactose, colloidal silicon dioxide, hypromellose, magnesium stearate, microcrystalline cellulose, polydextrose, polyethylene glycol, sodium lauryl sulfate, titanium dioxide, and triacetin

Questions?

Call 1-877-446-3679 (1-877-4-INFO-RX)

Manufactured for:
Mylan Pharmaceuticals Inc.
Morgantown, WV 26505

PACKAGE LABEL

PRINCIPAL DISPLAY PANEL - 5 mg Allergy

NDC 0378-3635-01

Cetirizine HCl
Tablets, USP
Allergy
5 mg
Antihistamine

Indoor & Outdoor Allergies

24 Hour Relief of

- runny nose
- sneezing
- itchy, watery eyes
- itching of the nose or throat

RMX-AR3635A 100 Tablets

Tamper Evident: do not use if foil seal
under cap is missing, open or broken.

PACKAGE LABEL

PRINCIPAL DISPLAY PANEL - 10 mg Allergy

NDC 0378-3637-01

Cetirizine HCl
Tablets, USP
Allergy
10 mg
Antihistamine

Indoor & Outdoor Allergies

24 Hour Relief of

- runny nose
- sneezing
- itchy, watery eyes
- itching of the nose or throat

RMX-AR3637A 100 Tablets

Tamper Evident: do not use if foil seal
under cap is missing, open or broken.

Active Ingredient (in each tablet)
Cetirizine hydrochloride USP, 10 mg

Directions
adults and children 6 years and over | one 10 mg tablet once daily; do not take more than one 10 mg tablet in 24 hours.; A 5 mg product may be appropriate for less severe symptoms.
adults 65 years and over | ask a doctor
children under 6 years of age | ask a doctor
consumers with liver or kidney disease | ask a doctor